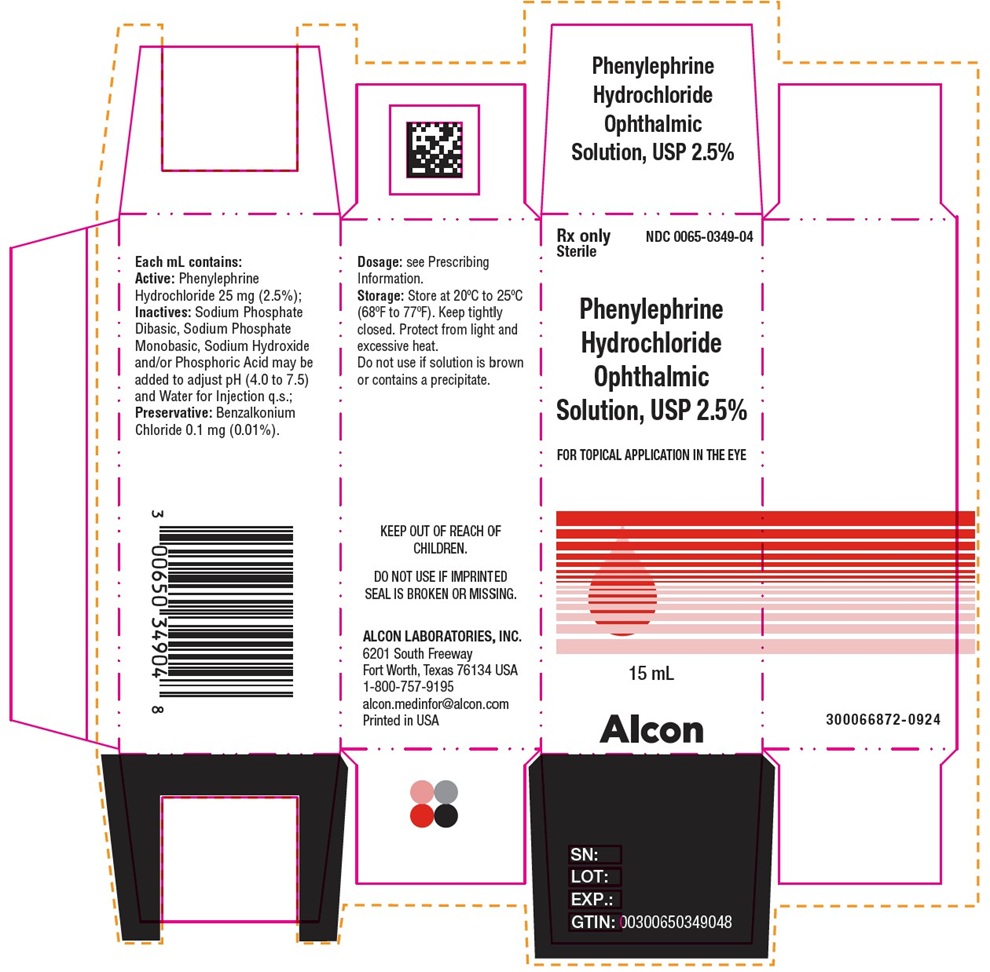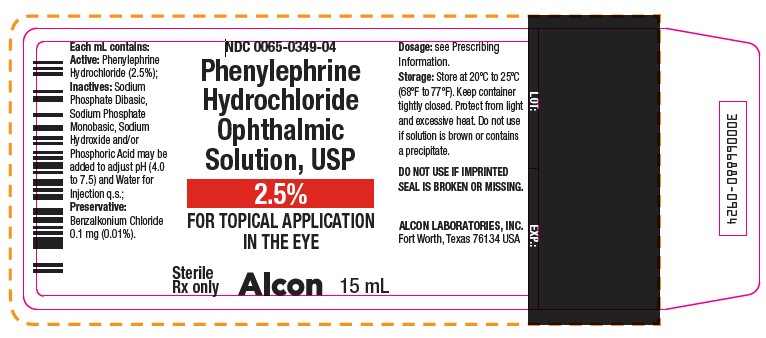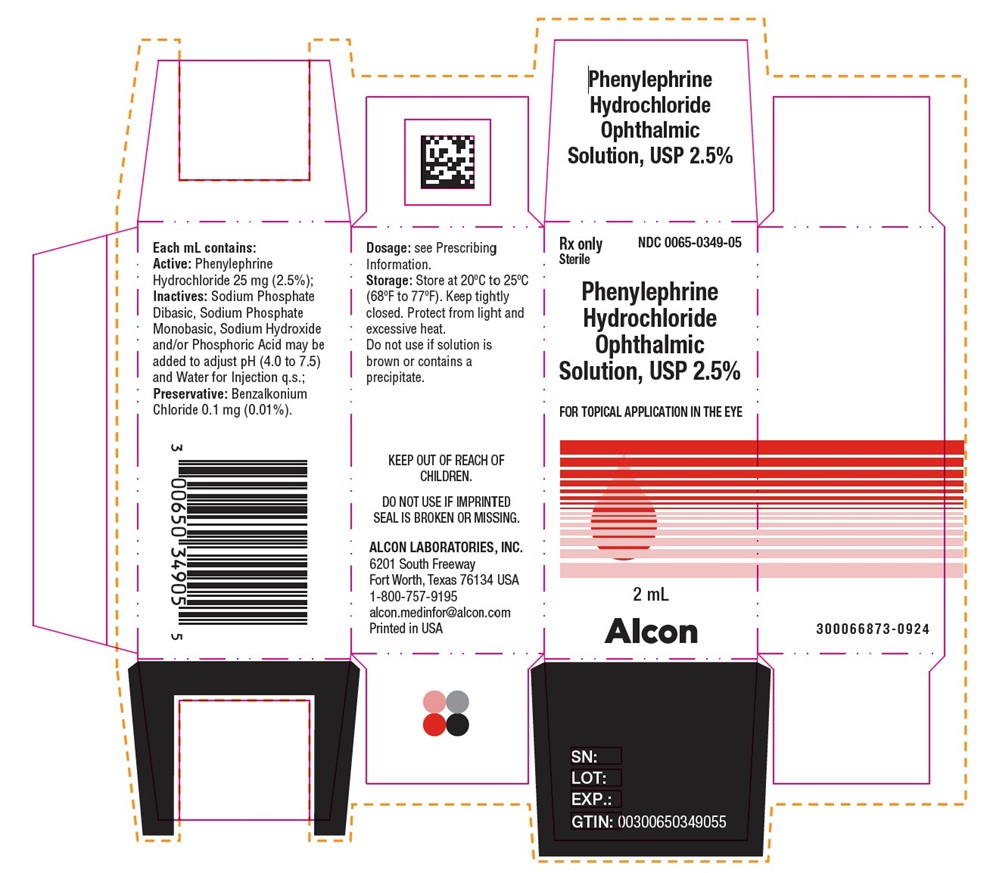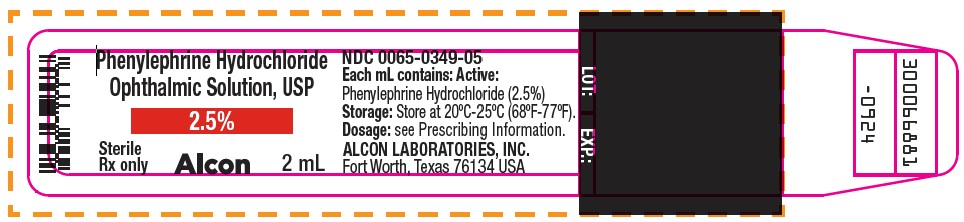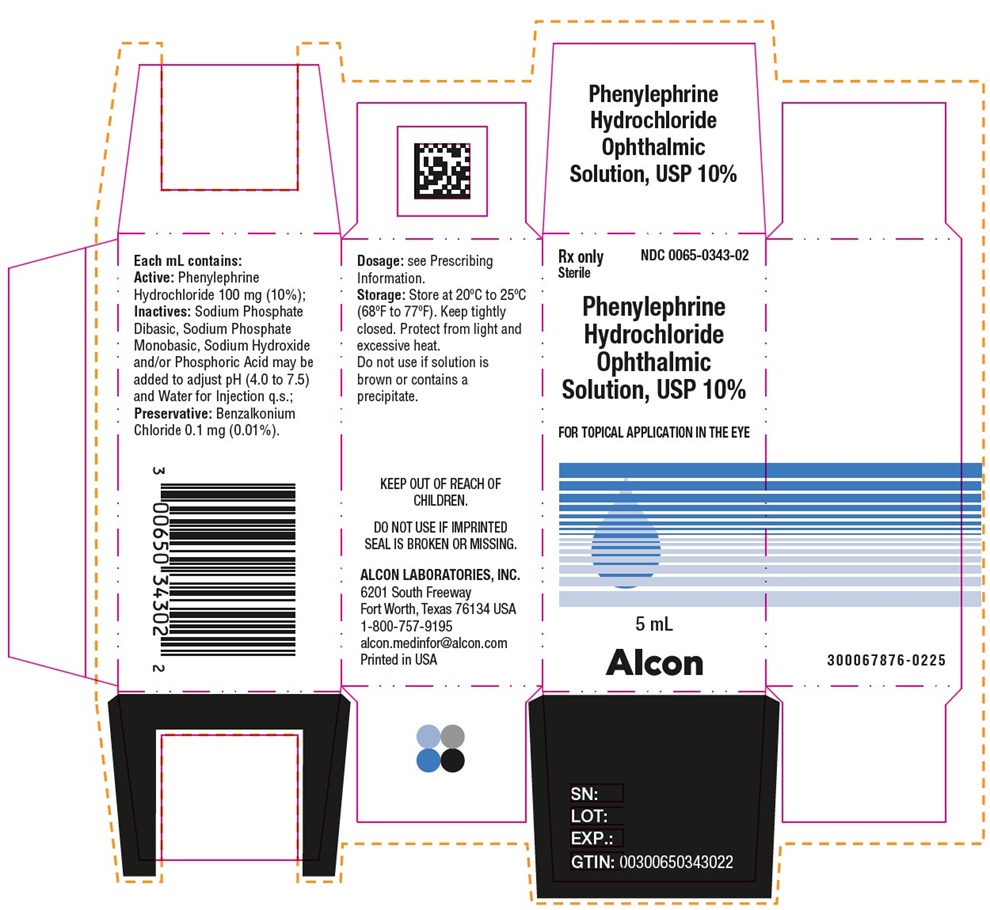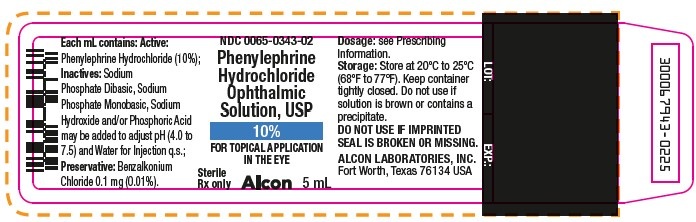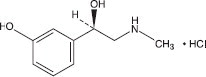 DRUG LABEL: Phenylephrine Hydrochloride
NDC: 0065-0349 | Form: SOLUTION/ DROPS
Manufacturer: Alcon Laboratories, Inc.
Category: prescription | Type: HUMAN PRESCRIPTION DRUG LABEL
Date: 20250401

ACTIVE INGREDIENTS: Phenylephrine Hydrochloride 25 mg/1 mL
INACTIVE INGREDIENTS: Sodium Phosphate, Dibasic, Anhydrous; Sodium Phosphate, Monobasic, Anhydrous; Sodium Hydroxide; Phosphoric Acid; Water; Benzalkonium Chloride

HIGHLIGHTS OF PRESCRIBING INFORMATION

These highlights do not include all the information needed to use PHENYLEPHRINE HYDROCHLORIDE OPHTHALMIC SOLUTION, USP safely and effectively. See full prescribing information for PHENYLEPHRINE HYDROCHLORIDE OPHTHALMIC SOLUTION, USP.
PHENYLEPHRINE HYDROCHLORIDE ophthalmic solution, USP 2.5% and 10%.
Initial U.S. Approval: 1939

1 INDICATIONS AND USAGE

Phenylephrine Hydrochloride Ophthalmic Solution is an alpha-1 adrenergic receptor agonist indicated to dilate the pupil (1)

2 DOSAGE AND ADMINISTRATION

For patients 1 year of age and older: (2.1)

- Apply one drop of Phenylephrine Hydrochloride Ophthalmic Solution (2.5% or 10% strength) to conjunctival fornix at 3 to 5 minute intervals up to a maximum of 3 drops per eye.
- To obtain a greater degree of mydriasis, use 10% strength

For pediatric patients less than 1 year of age: (2.2)

- Instill one drop of 2.5% strength to conjunctival fornix at 3 to 5 minute intervals up to a maximum of 3 drops per eye

3 DOSAGE FORMS AND STRENGTHS

Ophthalmic solution (sterile): (3)

- 25 mg of phenylephrine hydrochloride in one mL of solution (2.5%)
- 100 mg of phenylephrine hydrochloride in one mL of solution (10%)

4 CONTRAINDICATIONS

The 10% strength is contraindicated in:

- Patients with hypertension, or thyrotoxicosis (4.1)
- Pediatric patients less than 1 year of age due to increased risk of systemic toxicity (4.2)

5 WARNINGS AND PRECAUTIONS

- Not for injection: Topical ophthalmic use only (5.1)
- Serious cardiovascular reactions with 10% strength: Reactions have included ventricular arrhythmias and some have been fatal. Monitor blood pressure in patients with cardiovascular disease (5.2).
- Significant elevations in blood pressure: Caution in pediatric patients less than 5 years of age, and in patients with cardiovascular disease or hyperthyroidism. In patients at high risk, monitor blood pressure post treatment (5.3).
- Rebound miosis: Reported one day after instillation (5.4)

6 ADVERSE REACTIONS

- Ocular adverse reactions include eye pain and stinging on instillation, temporary blurred vision, and photophobia (6.1)
- Cardiovascular adverse reactions include increase in blood pressure, syncope, myocardial infarction, tachycardia, arrhythmia and subarachnoid hemorrhage (6.2)

To report SUSPECTED ADVERSE REACTIONS, contact Alcon Laboratories at 1-800-757-9195 or FDA at 1-800-FDA-1088 or www.fda.gov/medwatch

7 DRUG INTERACTIONS

- Atropine-like drugs: May exaggerate the adrenergic pressor response (7.1)
- Potent inhalation anesthetic agents: May potentiate cardiovascular depressant effects (7.1)

FULL PRESCRIBING INFORMATION

1 INDICATIONS AND USAGE

Phenylephrine Hydrochloride Ophthalmic Solution, USP 2.5% and 10%, is indicated to dilate the pupil.

2 DOSAGE AND ADMINISTRATION

2.1 General Dosing Recommendations

In patients 1 year of age or greater, apply one drop of either phenylephrine hydrochloride ophthalmic solution 2.5% or 10% every 3 to 5 minutes to the conjunctival fornix as required up to a maximum of 3 drops per eye per day.

In order to obtain a greater degree of mydriasis, phenylephrine hydrochloride ophthalmic solution 10% may be needed.

2.2 Dosing in Pediatric Patients Less Than 1 Year of Age

In pediatric patients less than 1 year of age, one drop of phenylephrine hydrochloride ophthalmic solution 2.5% should be instilled at 3 to 5 minute intervals up to a maximum of 3 drops per eye.

3 DOSAGE FORMS AND STRENGTHS

Phenylephrine hydrochloride ophthalmic solution, USP 2.5% is a clear, colorless to yellow, sterile topical ophthalmic solution containing phenylephrine hydrochloride 2.5%: each mL contains 25 mg of phenylephrine hydrochloride.

Phenylephrine hydrochloride ophthalmic solution, USP 10% is a clear, colorless to yellow, sterile topical ophthalmic solution containing phenylephrine hydrochloride 10%.: each mL contains 100 mg of phenylephrine hydrochloride.

4 CONTRAINDICATIONS

4.1 Cardiac and Endocrine Disease

Phenylephrine hydrochloride ophthalmic solution 10% is contraindicated in patients with hypertension or thyrotoxicosis. Phenylephrine hydrochloride ophthalmic solution 2.5% should be used in these patients.

4.2 Pediatric Patients Less Than 1 Year of Age

Phenylephrine hydrochloride ophthalmic solution 10% is contraindicated in pediatric patients less than 1 year of age due to the increased risk of systemic toxicity. Phenylephrine hydrochloride ophthalmic solution 2.5% should be used in these patients [See Dosage and Administration (2.2)].

5 WARNINGS AND PRECAUTIONS

5.1 Topical Ophthalmic Use Only

Phenylephrine hydrochloride ophthalmic solution 2.5% and 10% is not indicated for injection.

5.2 Cardiovascular Reactions

There have been reports of serious cardiovascular reactions, including ventricular arrhythmias and myocardial infarctions, in patients using phenylephrine 10%. These episodes, some fatal, have usually occurred in patients with pre-existing cardiovascular diseases. Phenylephrine Hydrochloride Ophthalmic Solution, USP 2.5% should be used in these patients.

5.3 Elevation of Blood Pressure

A significant elevation in blood pressure is not common but has been reported following conjunctival instillation of recommended doses of phenylephrine 10%. The risk is less with phenylephrine 2.5%. Caution should be exercised with the use of phenylephrine 10% in pediatric patients less than 5 years of age and patients with hyperthyroidism, or cardiovascular disease. The post-treatment blood pressure of patients with cardiac and endocrine diseases and any patients who develop symptoms should be carefully monitored.

5.4 Rebound Miosis

Rebound miosis has been reported one day after receiving phenylephrine hydrochloride ophthalmic solution, and re-instillation of the drug produced a lesser mydriatic effect.

6 ADVERSE REACTIONS

The following serious adverse reactions are described below and elsewhere in the labeling:

- Cardiovascular Effects [See Warnings and Precautions (5.2)]
- Elevation in Blood Pressure [See Warnings and Precautions (5.3)]

The following adverse reactions have been identified following use of phenylephrine hydrochloride ophthalmic solution. Because these reactions are reported voluntarily from a population of uncertain size, it is not always possible to reliably estimate their frequency or establish a causal relationship to drug exposure.

6.1 Ocular Adverse Reactions

Eye pain and stinging on instillation, temporary blurred vision and photophobia, and conjunctival sensitization may occur.

6.2 Systemic Adverse Reactions

A marked increase in blood pressure has been reported particularly, but not limited to low weight premature neonates, infants and hypertensive patients.

Cardiovascular effects which have been seen primarily in hypertensive patients following topical ocular use of phenylephrine hydrochloride ophthalmic solution 10% include marked increase in blood pressure, syncope, myocardial infarction, tachycardia, arrhythmia and subarachnoid hemorrhage [See Warnings and Precautions (5.2 and 5.3)].

7 DRUG INTERACTIONS

7.1 Agents That May Exaggerate Pressor Responses

Concomitant use of phenylephrine and atropine may enhance the pressor effects and induce tachycardia in some patients. Phenylephrine may potentiate the cardiovascular depressant effects of some inhalation anesthetic agents.

8 USE IN SPECIFIC POPULATIONS

8.1 Pregnancy

Animal reproduction studies have not been conducted with topical phenylephrine. It is also not known whether phenylephrine can cause fetal harm when administered to a pregnant woman or can affect reproduction capacity. Phenylephrine hydrochloride should be given to a pregnant woman only if clearly needed.

8.3 Nursing Mothers

It is not known whether this drug is excreted in human breast milk. Because many drugs are excreted in human milk, caution should be exercised when phenylephrine hydrochloride ophthalmic solution 2.5% and 10% is administered to a nursing woman.

8.4 Pediatric Use

Phenylephrine hydrochloride ophthalmic solution 10% is contraindicated in pediatric patients less than 1 year of age [See Contraindications (4.2)].

8.5 Geriatric Use

No overall differences in safety and effectiveness have been observed between elderly and younger adult patients.

10 OVERDOSAGE

Overdosage of phenylephrine may cause a rapid rise in blood pressure. It may also cause headache, anxiety, nausea, and vomiting, and ventricular arrhythmias. Prompt injection of a rapidly acting alpha-adrenergic blocking agent such as phentolamine has been recommended.

11 DESCRIPTION

Phenylephrine Hydrochloride Ophthalmic Solution, USP is a sterile, clear, colorless to yellow, topical α-adrenergic agonist for ophthalmic use. The active ingredient is represented by the chemical structure

Chemical Name: (R)-3-hydroxy-α[(methylamino)methyl]benzenemethanol hydrochloride.

Molecular Formula: C9H13NO2.HCl

Molecular Weight: 203.67 g/mol

Each mL of Phenylephrine Hydrochloride Ophthalmic Solution, USP 2.5% contains: ACTIVE: Phenylephrine Hydrochloride 25 mg (2.5%); INACTIVES: Sodium Phosphate Monobasic, Sodium Phosphate Dibasic, Water for Injection. Phosphoric Acid and/or Sodium Hydroxide may be added to adjust pH (4.0 to 7.5). The solution has a tonicity of 340 mOsm/kg; PRESERVATIVE: Benzalkonium Chloride 0.1 mg (0.01%).

Each mL of Phenylephrine Hydrochloride Ophthalmic Solution, USP 10% contains: ACTIVE: Phenylephrine Hydrochloride 100 mg (10%); INACTIVES: Sodium Phosphate Monobasic, Sodium Phosphate Dibasic, Water for Injection. Phosphoric Acid and/or Sodium Hydroxide may be added to adjust pH (4.0 to 7.5). The solution has a tonicity of 985 mOsm/kg; PRESERVATIVE: Benzalkonium Chloride 0.1 mg (0.01%).

12 CLINICAL PHARMACOLOGY

12.1 Mechanism of Action

Phenylephrine hydrochloride is an α-1 adrenergic agonist drug that is used in ophthalmology mainly for its mydriatic effect. After topical application to the conjunctiva, phenylephrine acts directly on α-adrenergic receptors in the eye, producing contraction of the dilator muscle of the pupil and constriction of the arterioles in the conjunctiva.

12.2 Pharmacodynamics

Maximal mydriasis occurs in 20 to 90 minutes with recovery after 3 to 8 hours.

Systemic absorption of sufficient quantities of phenylephrine may lead to systemic α-adrenergic effects, such as rise in blood pressure which may be accompanied by a reflex atropine-sensitive bradycardia.

12.3 Pharmacokinetics

The systemic exposure following topical administration of phenylephrine hydrochloride ophthalmic solution has not been studied. A higher systemic absorption is expected for the 10% solution than the 2.5% solution and when the corneal barrier function is compromised.

14 CLINICAL STUDIES

Pupillary dilation following topical administration of phenylephrine hydrochloride ophthalmic solution has been demonstrated in controlled clinical studies in adults and pediatric patients with different levels of iris pigmentation. Pupil movement is generally seen within 15 minutes, maximal mydriasis between 20 to 90 minutes and recovery after 3 to 8 hours. Darker irides tend to dilate slower than lighter irides.

16 HOW SUPPLIED/STORAGE AND HANDLING

Phenylephrine Hydrochloride Ophthalmic Solution, USP 2.5% is supplied as a sterile, aqueous, topical ophthalmic solution in an opaque, white low density polyethylene (LDPE) bottle with a natural LDPE dropper tip and red cap in the following sizes:

NDC 0065-0349-05 2 mL in 4 mL bottle
NDC 0065-0349-04 15 mL in 15 mL bottle

Phenylephrine Hydrochloride Ophthalmic Solution, USP 10% is supplied as a sterile, aqueous, topical ophthalmic solution in an opaque, white low density polyethylene (LDPE) bottle with a natural LDPE dropper tip and red cap in the following sizes:

NDC 0065-0343-02 5 mL in 8 mL bottle

After opening, Phenylephrine Hydrochloride Ophthalmic Solution, USP can be used until the expiration date on the bottle.

STORAGE AND HANDLING

Storage: Store at 20°C to 25°C (68°F to 77°F).

Keep container tightly closed.

Protect from light and excessive heat.

Do not use if solution is brown or contains precipitate.

17. PATIENT COUNSELING INFORMATION

Advise patients not to touch the dropper tip to any surface as this may contaminate the solution. Inform patients that they may experience sensitivity to light and should protect their eyes in bright illumination while their pupils are dilated.

Distributed by: ALCON LABORATORIES, INC.
Fort Worth, Texas 76134 U.S.A.

Principal Display Panel Text for Container Label:

Phenylephrine Hydrochloride
Ophthalmic Solution, USP
2.5%
Sterile
Rx only
Alcon
2mL
NDC 0065-0349-05
Each mL contains: Active:
Phenylephrine Hydrochloride (2.5%)
Storage: Store at 20ºC-25ºC (68ºF-77ºF).
Dosage: see Prescribing Information
ALCON LABORATORIES, INC.
Fort Worth, Texas 76134 USA
LOT: EXP.:
300066881-0924

Principal Display Panel Text for Carton Label:

Rx only
Sterile
NDC 0065-0349-05
Phenylephrine
Hydrochloride
Ophthalmic
Solution, USP 2.5%
FOR TOPICAL APPLICATION IN THE EYE
2mL
Alcon
Each mL contains:
Active: Phenylephrine
Hydrochloride 25 mg (2.5%);
Inactives: Sodium Phosphate
Dibasic, Sodium Phosphate
Monobasic, Sodium Hydroxide
and/or Phosphoric Acid may be
added to adjust pH (4.0 to 7.5)
and Water for Injection q.s.;
Preservative: Benzalkonium
Chloride 0.1 mg (0.01%).
Dosage: see Prescribing
Information.
Storage: Store at 20ºC to 25ºC
(68ºF to 77ºF). Keep tightly
closed. Protect from light and
excessive heat.
Do not use if solution is
brown or contains a
precipitate.
KEEP OUT OF REACH OF
CHILDREN.
DO NOT USE IF IMPRINTED
SEAL IS BROKEN OR MISSING.
ALCON LABORATORIES, INC.
6201 South Freeway
Fort Worth, Texas 76134 USA
1-800-757-9195
alcon.medinfor@alcon.com
Printed in USA
300066873-0924
SN:
LOT:
EXP.:
GTIN: 00300650349055

Principal Display Panel Text for Container Label:

NDC 0065-0349-04
15mL
300066880-0924

Principal Display Panel Text for Carton Label:

NDC 0065-0349-04
15mL
300066872-0924
SN:
LOT:
EXP.:
GTIN: 00300650349048

Principal Display Panel Text for Container Label:
NDC 0065-0343-02
Phenylephrine
Hydrochloride
Ophthalmic
Solution, USP
10%
FOR TOPICAL APPLICATION
IN THE EYE
Sterile Rx
only
Alcon
5 mL
Each mL contains: Active:
Phenylephrine Hydrochloride (10%);
Inactives: Sodium
Phosphate Dibasic, Sodium
Phosphate Monobasic, Sodium
Hydroxide and/or Phosphoric Acid
may be added to adjust pH (4.0 to
7.5) and Water for Injection q.s.;
Preservative: Benzalkonium
Chloride 0.1 mg (0.01%).
Dosage: see Prescribing
Information.
Storage: Store at 20ºC to 25ºC
(68ºF to 77ºF). Keep container
tightly closed. Do not use if
solution is brown or contains a
precipitate.
DO NOT USE IF IMPRINTED
SEAL IS BROKEN OR MISSING.
ALCON LABORATORIES, INC.
Fort Worth, Texas 76134 USA
LOT: EXP.:
30006 7943-0225

Principal Display Panel Text for Carton Label:
NDC 0065-343-02
KEEP OUT OF REACH OF
CHILDREN
ALCON LABORATORIES, INC.
6201 South Freeway
Fort Worth, Texas 76134 USA
1-800-757-9195
alcon.medinfor@alcon.com
Printed in USA
SN:
LOT:
EXP.:
GTIN: 00300650343022
300067876-0225